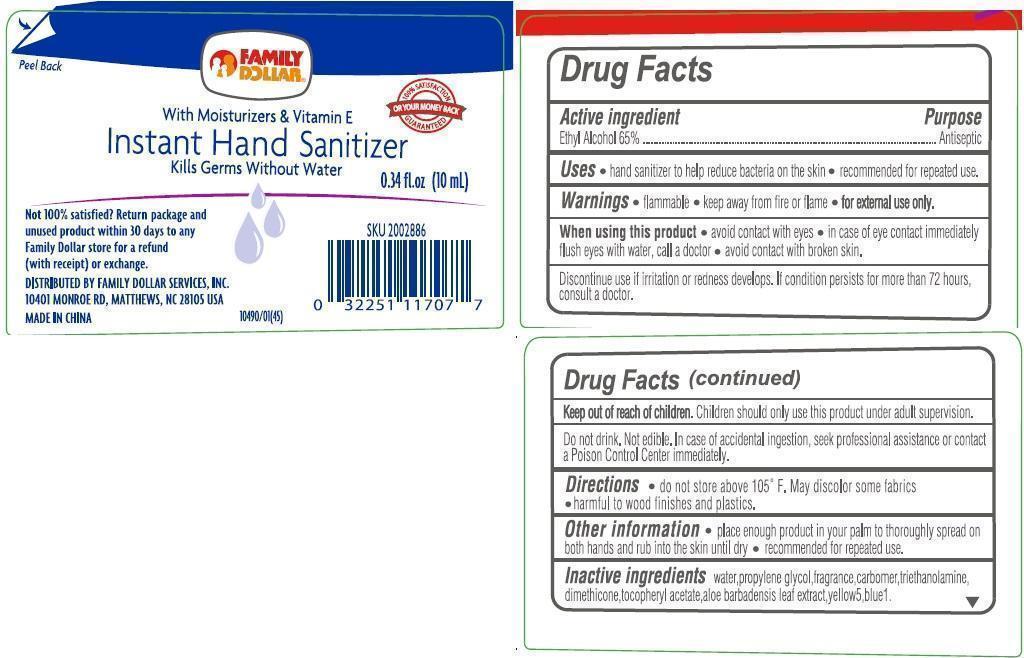 DRUG LABEL: Family Dollar Instant Hand Sanitizer with Moisturizers and Vitamin E
NDC: 40104-520 | Form: GEL
Manufacturer: Ningbo Pulisi Daily Chemical Products Co., Ltd.
Category: otc | Type: HUMAN OTC DRUG LABEL
Date: 20141020

ACTIVE INGREDIENTS: ALCOHOL 65 mL/100 mL
INACTIVE INGREDIENTS: CAPRYLYL GLYCOL; GLYCERIN; ISOPROPYL ALCOHOL; ISOPROPYL MYRISTATE; POLYOXYL 40 HYDROGENATED CASTOR OIL; PHENOXYETHANOL; PROPYLENE GLYCOL; ALPHA-TOCOPHEROL ACETATE; TROLAMINE; WATER

Drug Facts

Active ingredient
Ethyl Alcohol 65% v/v

Purpose
Antiseptic

INDICATIONS AND USAGE

Uses • hand sanitizer to help reduce bacteria on the skin. • recommended for repeated use

WARNINGS

Warnings • Flammable • Keep away from fire or flame • For external use only

When using this product • avoid contact with eyes • in case of eye contact immediately flush eyes with water, call a doctor • avoid contact with broken skin

Discontinue use if irritation or redness develops. If condition persists for more than 72 hours, consult a doctor.

Keep out of reach of children. Children should only use this product under adult supervision.

Do not drink. Not edible in case of accidental ingestion seek professional assistance or contact a Poison Control Center right away.

Other Information •do not store above 105F. May discolor some fabrics • harmful to wood finishes and plastics

DOSAGE AND ADMINISTRATION

Directions •place enough product in your palm to thoroughly spread on both hands and rub into the skin until dry • recommended for repeated use.

INACTIVE INGREDIENT

Inactive ingredients caprylyl glycol, carbomer, fragrance, glycerin, isopropyl alcohol, isopropyl myristate, PEG-40 hydrogenated castor oil, phenoxyethanol, propylene glycol, tocopheryl acetate, triethanolamine, water.